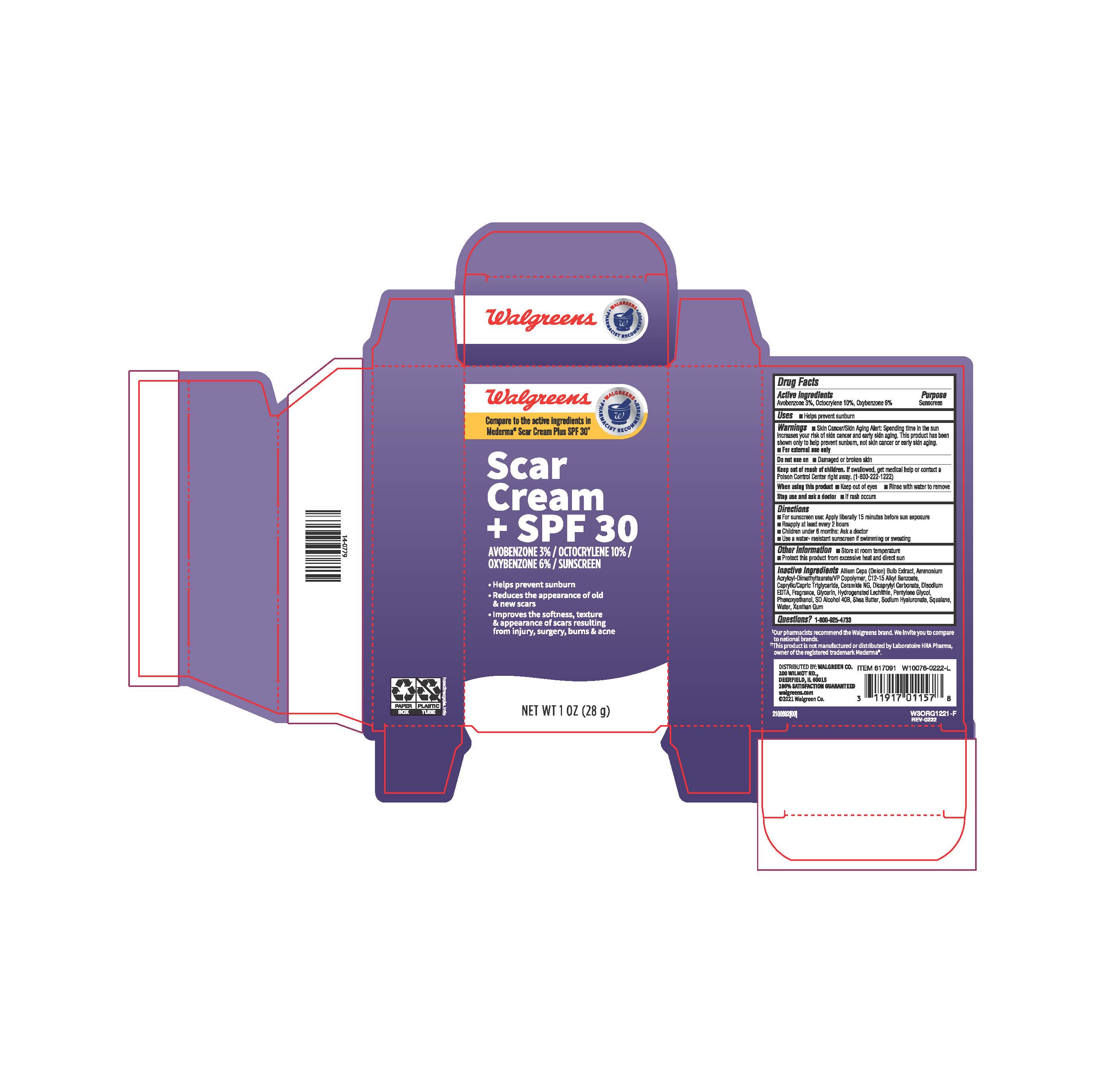 DRUG LABEL: Walgreens Scar Cream w/SPF 30
NDC: 0363-2054 | Form: CREAM
Manufacturer: Walgreens
Category: otc | Type: HUMAN OTC DRUG LABEL
Date: 20241211

ACTIVE INGREDIENTS: OCTOCRYLENE 100 mg/1 g; OXYBENZONE 60 mg/1 g; AVOBENZONE 30 mg/1 g
INACTIVE INGREDIENTS: WATER; DEHYDRATED ALCOHOL; ALKYL (C12-15) BENZOATE; GLYCERIN; HYALURONATE SODIUM; ONION; CERAMIDE NG; HYDROGENATED SOYBEAN LECITHIN; SHEA BUTTER; MEDIUM-CHAIN TRIGLYCERIDES; PENTYLENE GLYCOL; PHENOXYETHANOL; AMMONIUM ACRYLOYLDIMETHYLTAURATE/VP COPOLYMER; DICAPRYLYL CARBONATE; SQUALANE; XANTHAN GUM; EDETATE DISODIUM

ACTIVE INGREDIENT

Avobenzone 3%

Octocrylene 10%

Oxybenzone 6%

PURPOSE

Sunscreen

INDICATIONS AND USAGE

Helps prevent sunburn

WARNINGS

For External use only

Do not use on: Damaged or broken skin

KEEP OUT OF REACH OF CHILDREN

If swallowed, get medical help or contact a Poison Control Center right away. (1-800-222-1222)

WHEN USING

Keep out of eyes

Rinse with water to remove

Stop use and ask a doctor:

If rash occurs

DOSAGE AND ADMINISTRATION

For Sunscreen use: Apply liberally 15 minutes before exposure

Reapply at least 2 hours

Children under 6 months : Ask a doctor

Use a water - resistant sunscreen if swimming or sweating

OTHER SAFETY INFORMATION

Store at room temperature

Protect this product from excessive heat and direct sun

INACTIVE INGREDIENT

Allium Cepa (Onion) Bulb Extract, Ammonium Acryloyl- Dimethyltaurate/VP Copolymer, C12-15 Alkyl Benzoate, Capryl/Capric Triglyceride, Ceramide NG, Dicaprylyl Carbonate, Disodium EDTA, Fragrance, Glycerin, Hyrogenated Lechithin, Pentylene Glycol, Phenoxyethanol, SD Alcohol 40 B, Shea Butter, Sodium Hyaluronate, Squalane, Water, Xanthan Gum

QUESTIONS

1-800-925-4733